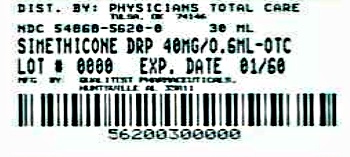 DRUG LABEL: Simethicone
NDC: 54868-5620 | Form: SOLUTION/ DROPS
Manufacturer: Physicians Total Care, Inc.
Category: otc | Type: HUMAN OTC DRUG LABEL
Date: 20120502

ACTIVE INGREDIENTS: DIMETHICONE 63.3 mg/1 mL; SILICON DIOXIDE 3.7 mg/1 mL
INACTIVE INGREDIENTS: CARBOMER HOMOPOLYMER TYPE B; ANHYDROUS CITRIC ACID; FD&C RED NO. 3; HYPROMELLOSES; WATER; SACCHARIN SODIUM; SODIUM BENZOATE; SODIUM CITRATE

Infants Simethicone Drops

Active ingredient (in each 0.3 mL)

Simethicone 20 mg

Purpose

Anti-gas

Uses

Relieves the discomfort of infant gas frequently caused by air swallowing or certain formulas or foods.

Keep out of reach of children.

In case of overdose, get medical help or contact a Poison Control Center right away.

Directions

- shake well before using
- all dosages may be repeated as needed, after meals and at bedtime or as directed by a physician. Do not exceed 12 doses per day.
- fill enclosed dropper to recommended dosage level and dispense liquid slowly into baby’s mouth, toward the inner cheek
- dosage can also be mixed with 1 oz of cool water, infant formula or other suitable liquids
- for best results, clean dropper after each use and replace original cap

Age | Weight | Dose
newborn | - - - - | 0.3 mL
infants under 2 years | under 24 lbs | 0.3 mL
children over 2 years | over 24 lbs | 0.6 mL

Other information

- store at room temperature 15°- 30°C (59°- 86°F)
- do not freeze

You may report serious side effects to: 130 Vintage Drive, Huntsville, AL 35811.

Inactive ingredients

carbomer, citric acid, FD&C red #3, flavor, hypromellose, purified water, saccharin sodium, sodium benzoate, sodium citrate

Made in the USA
for Qualitest Pharmaceuticals
Huntsville, AL 35811

Rev. 6/10 R6
8276455 0894

Additional barcode labeling by:
Physicians Total Care, Inc.
Tulsa, Oklahoma 74146